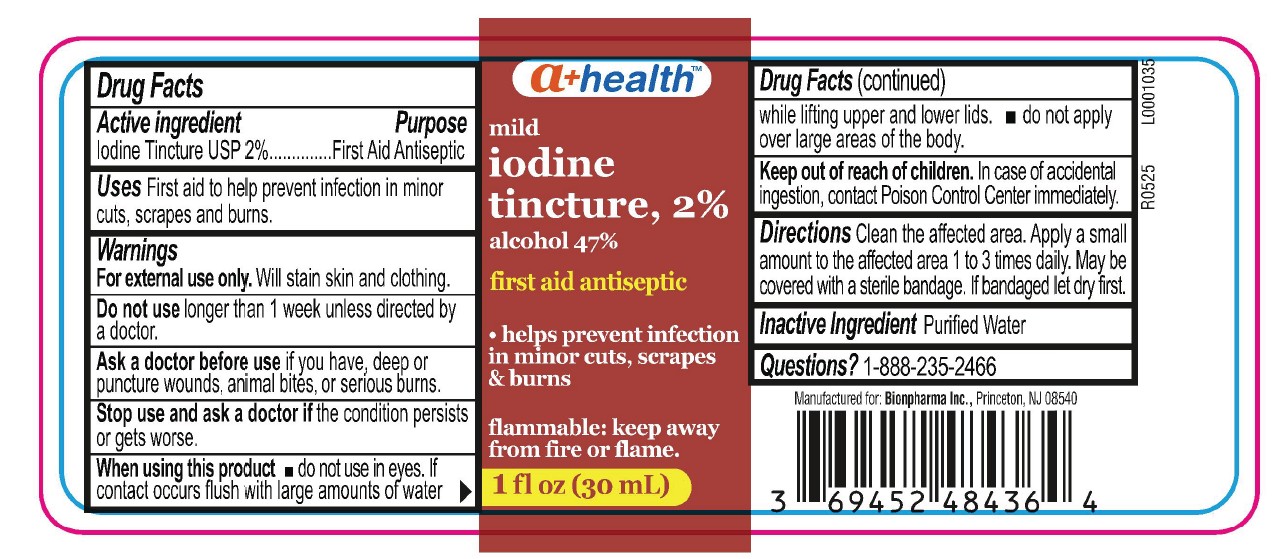 DRUG LABEL: mild iodine tincture
NDC: 69452-484 | Form: LIQUID
Manufacturer: BIONPHARMA INC.
Category: otc | Type: HUMAN OTC DRUG LABEL
Date: 20251006

ACTIVE INGREDIENTS: IODINE 20 mg/1 mL; ALCOHOL 470 mg/1 mL; SODIUM IODIDE 20.4 mg/1 mL
INACTIVE INGREDIENTS: WATER

A+ Health-Iodine tincture mild

Active ingredient

IodineTincture USP 2%

Purpose

First Aid Antiseptic

Uses

First aid to help prevent infection in minor cuts, scrapes and burns.

Warnings

For external use only. Will stain skin and clothing.

Do not use longer than 1 week unless directed by a doctor.

Ask a doctor before use if you have, deep or punture wounds, animal bites, or serious burns.

Stop use and ask a doctor if

the condition persists or gets worse.

When using this product

■ do not use in eyes. If contact occurs flush with large amounts of water while lifting upper and lower lids. ■ do not apply over large areas of the body.

Keep out of reach of children.

In case of accidental ingestion, contact Poison Control Center immediately.

Directions

Clean the affected area. Apply a small amount to the affected area 1 to 3 times daily. May be covered with a sterile bandage. If bandaged let dry first.

Inactive Ingredient

Purified Water

Questions?

1-888-235-2466

Manufactured for: Bionpharma Inc., Princeton, NJ 08540

R0525 L0001035

1 fl oz. bottle label

a+ healthTM

mild

iodine

tincture, 2%

alcohol 47%

first aid antiseptic

- helps prevent infection in minor cuts, scrapes & burns

flammable: Keep away

from fire or flame.

1 fl oz (30 mL)